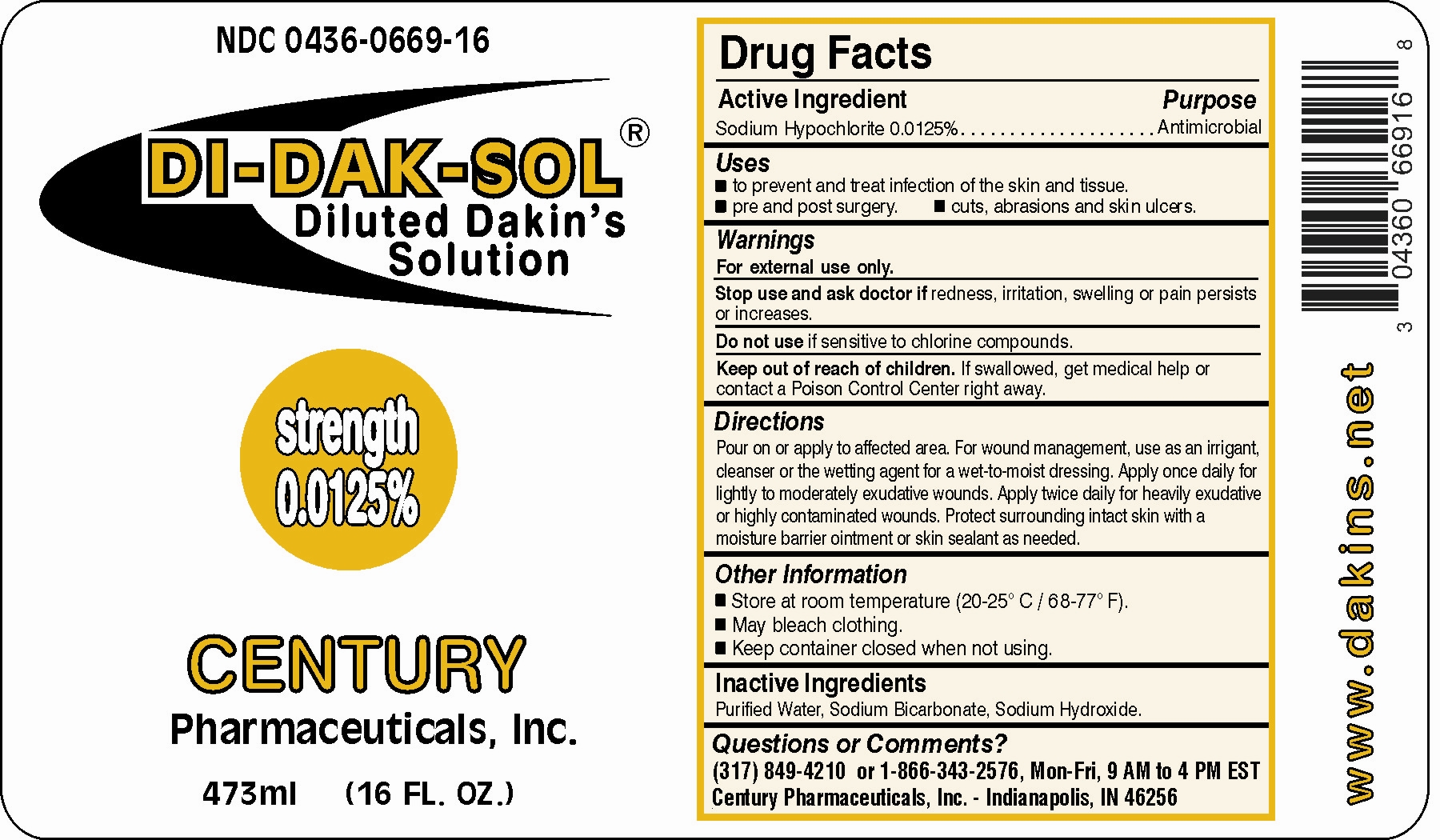 DRUG LABEL: Di-Dak-Sol								
NDC: 0436-0669 | Form: SOLUTION
Manufacturer: Century Pharmaceuticals, Inc.
Category: otc | Type: HUMAN OTC DRUG LABEL
Date: 20260217

ACTIVE INGREDIENTS: SODIUM HYPOCHLORITE 0.125 mg/1 mL
INACTIVE INGREDIENTS: SODIUM HYDROXIDE; SODIUM BICARBONATE; WATER

Di-Dak-Sol (Sodium Hypochlorite 0.0125%)

ACTIVE INGREDIENT

Sodium Hypochlorite 0.0125%

PURPOSE

Antimicrobial

Uses

To prevent and treat infection of the skin and tissue.
Pre and post surgery Cuts, abrasions and skin ulcers

WARNINGS

For external use only.

Stop use and ask a doctor if redness, irritation, swelling or pain persists or increases.

Do not use if sensitive to chlorine compounds.

Keep out of reach of children.

If swallowed, get medical help or contact a Poison Control Center right away.

Directions

Pour on or apply to affected area. For wound management, use as an irrigant,
cleanser, or the wetting agent for a wet-to-moist dressing. Apply once daily for
lightly to moderately exudative wounds. Apply twice daily for highly exudative
or highly contaminated wounds. Protect surrounding intact skin with a moisture
barrier ointment or skin sealant as needed.

Other Information

Store at room temperature.

May bleach clothing.

Keep container closed when not using.

INACTIVE INGREDIENT

Purified Water, Sodium Bicarbonate,Sodium Hydroxide.

Questions or Comments?
(317) 849-4210 or 1-866-343-2576, Mon-Fri, 9AM to 4PM EST
Century Pharmaceuticals, Inc. - Indianapolis, IN 46256

PACKAGE LABEL

Enter section text here